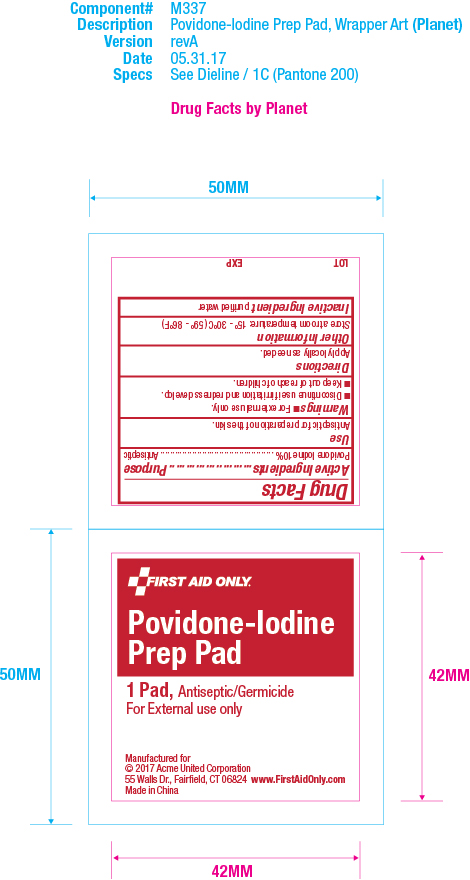 DRUG LABEL: First Aid Only Povidone-Iodine Prep Pad
NDC: 0924-8110 | Form: PATCH
Manufacturer: Acme United Corporation
Category: otc | Type: HUMAN OTC DRUG LABEL
Date: 20241109

ACTIVE INGREDIENTS: POVIDONE-IODINE 10 g/100 g
INACTIVE INGREDIENTS: WATER

First Aid Only Povidone-Iodine Prep Pad

Active Ingredients

Active Ingredients Povidone Iodine 10%

Purpose

Purpose Antiseptic

Use

Use Antispetic for preparation of the skin.

Warnings

Warnings •For external use only.

•Discontinue use if irritation and redness develop.

•Keep out of reach of children.

Keep out of reach of children. If swallowed get medical help or contact a Poison Control Center right away.

Directions

Directions Apply locally as needed.

Other Information

Other Information Store at room temperature 15° - 30°C (59° - 86°F)

Inactive Ingredient

Inactive Ingredient purified water